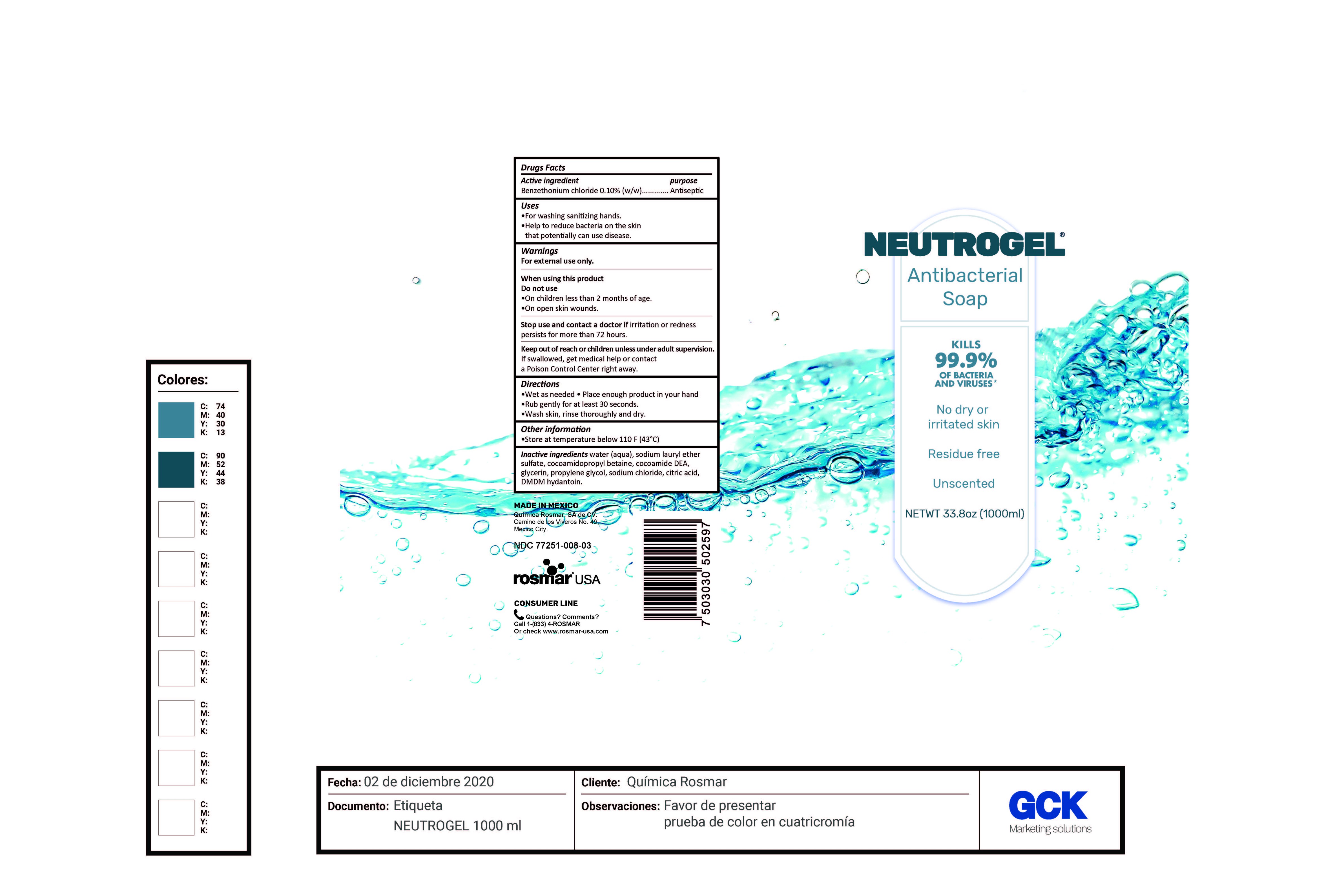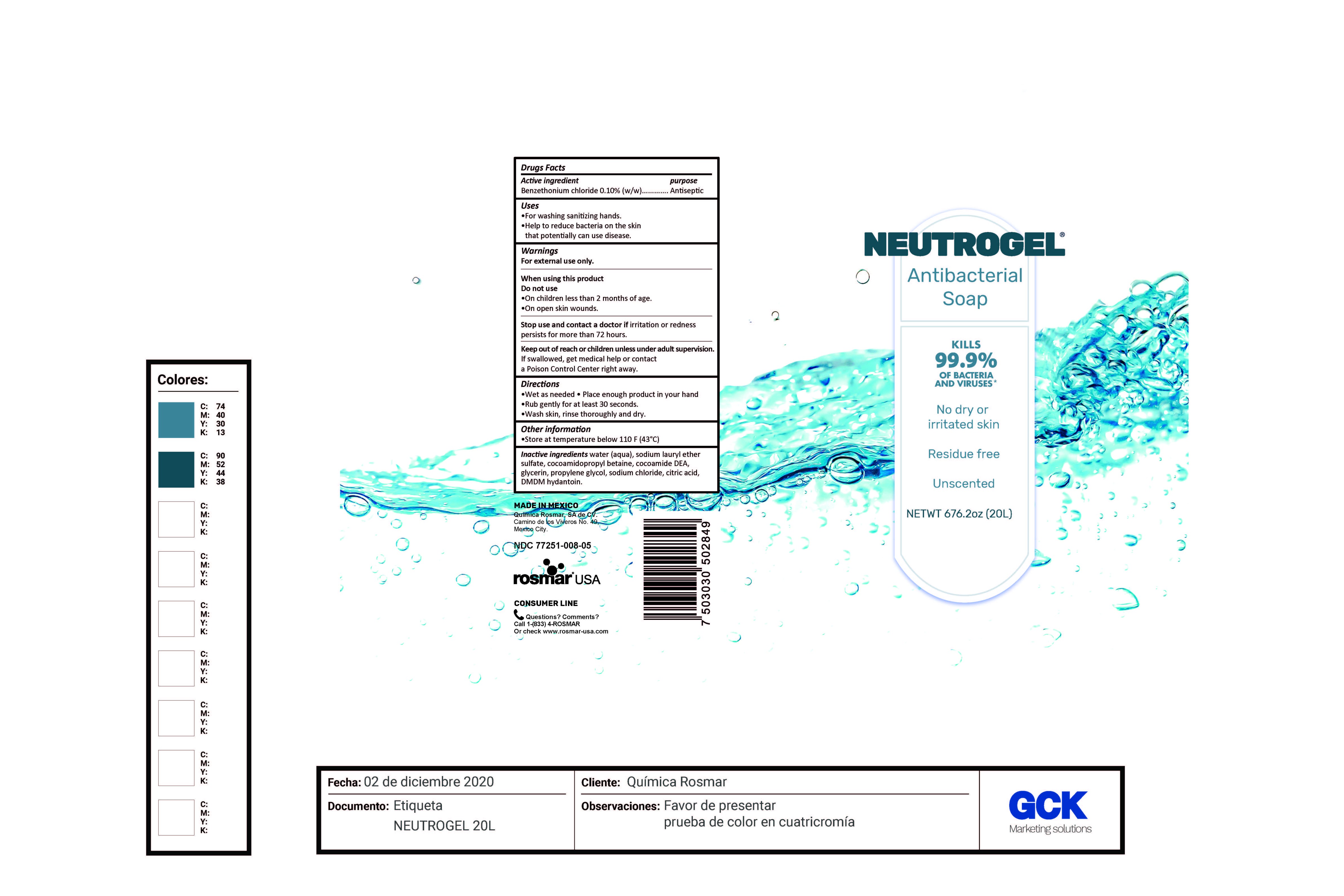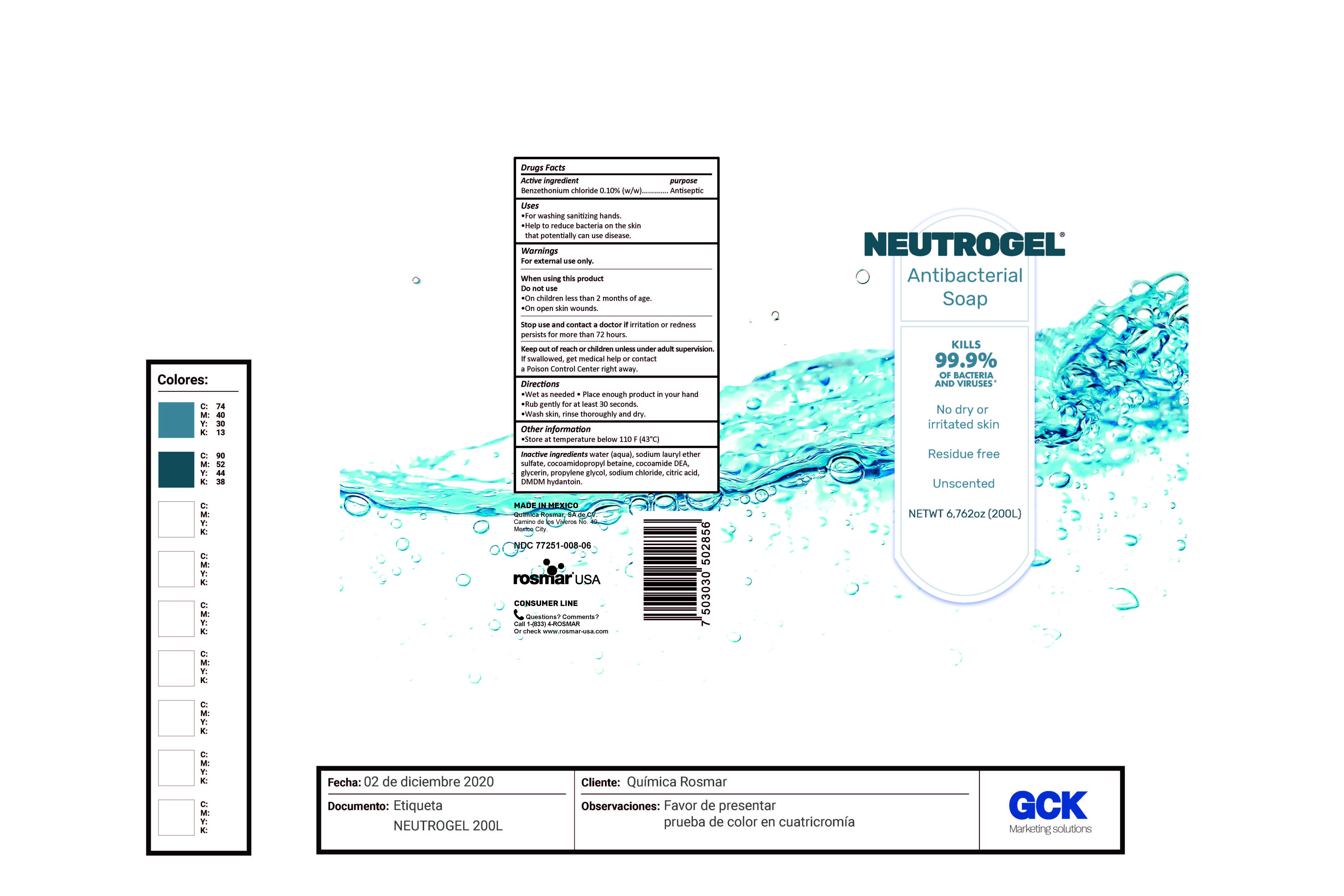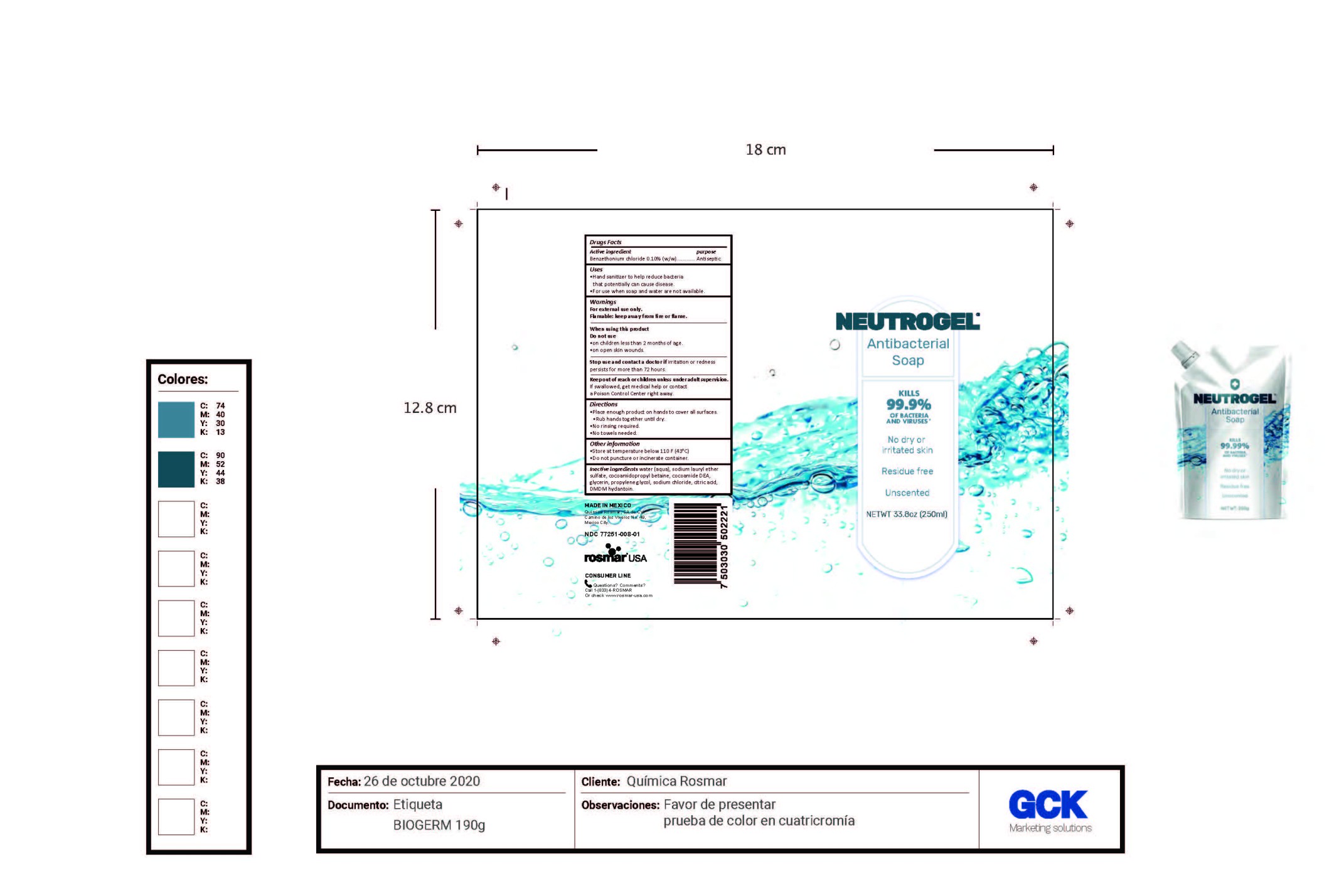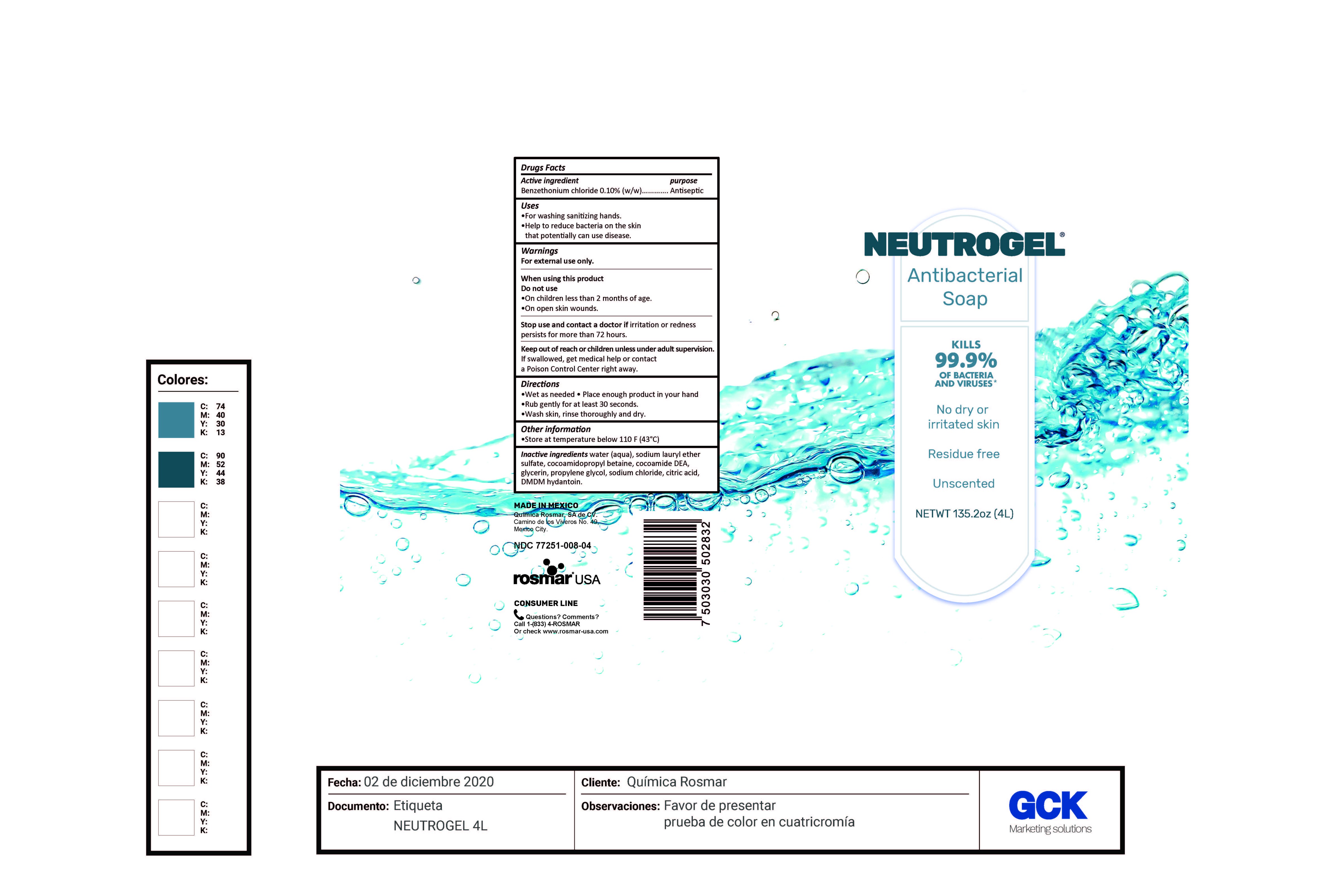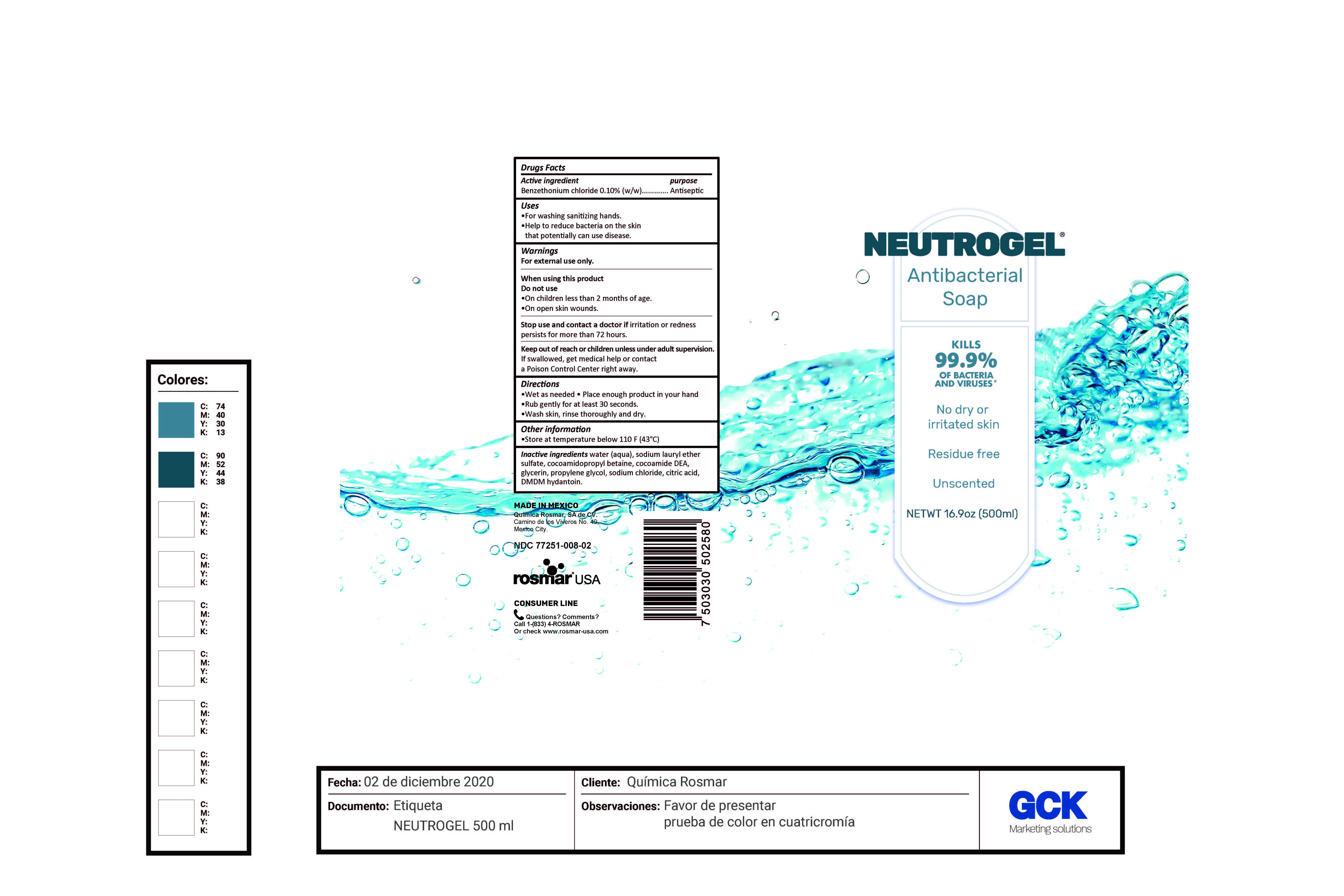 DRUG LABEL: Neutrogel
NDC: 77251-008 | Form: GEL
Manufacturer: QUIMICA ROSMAR S.A DE C.V
Category: otc | Type: HUMAN OTC DRUG LABEL
Date: 20210112

ACTIVE INGREDIENTS: BENZETHONIUM CHLORIDE 0.1 mg/100 mL
INACTIVE INGREDIENTS: COCO DIETHANOLAMIDE; WATER; GLYCERIN; SODIUM LAURETH SULFATE; DMDM HYDANTOIN; ANHYDROUS CITRIC ACID; PROPYLENE GLYCOL; SODIUM CHLORIDE; COCAMIDOPROPYL BETAINE

77251-008 Neutrogel
Benzethonium chloride 0.10%

This is a hand sanitizer manufactured according to the Temporary Policy for Preparation of Certain Alcohol-Based Hand Sanitizer Products During the Public Health Emergency (CoViD-19); Guidance for Industry.

The hand sanitizer is manufactured using only the following United States Pharmacopoeia (USP) grade ingredients in the preparation of the product (percentage in final product formulation) consistent with World Health Organization (WHO) recommendations:

1. Alcohol (ethanol) (USP or Food Chemical Codex (FCC) grade) (80%, volume/volume (v/v)) in an aqueous solution denatured according to Alcohol and Tobacco Tax and Trade Bureau regulations in 27 CFR part 20.
2. Glycerol (1.45% v/v).
3. Hydrogen peroxide (0.125% v/v).
4. Sterile distilled water or boiled cold water.

The firm does not add other active or inactive ingredients. Different or additional ingredients may impact the quality and potency of the product.

Active Ingredient(s)

Benzethonium chloride 0.10% w/w. Purpose: Antiseptic

Purpose

Antiseptic

Use

- For washing sanitizing hands
- Helps reduce bacteria on the skin that potentially can cause disease

Warnings

For external use only.

Do not use

- in children less than 2 months of age
- on open skin wounds

When using this product do not use

- On children less than 2 months of age
- On open skin wounds

Stop use and ask a doctor if irritation or redness persists for more than 72 hours.

Keep out of reach of children. If swallowed, get medical help or contact a Poison Control Center right away.

Directions

- Wet as needed
- Place enough product in your hand
- Rub gently for at leats 30 seconds
- Wash skin, rinse thoroughly and dry

Other information

- Store at temperature below 110F (43C)

Inactive ingredients

water, sodium lauryl ether sulfate, cocamidopropyl betaine, cocamide DEA, glycerin, propylene glycol, sodium chloride, citric acid, DMDM hydantoin

Package Label - Principal Display Panel

4000 mL NDC: 77251-008-01

200000 mL NDC: 77251-008-02

20000 mL NDC : 77251-008-03

1000 mL NDC: 77251-008-04

500 mL NDC: 77251-008-05

250 mL NDC: 77251-008-06